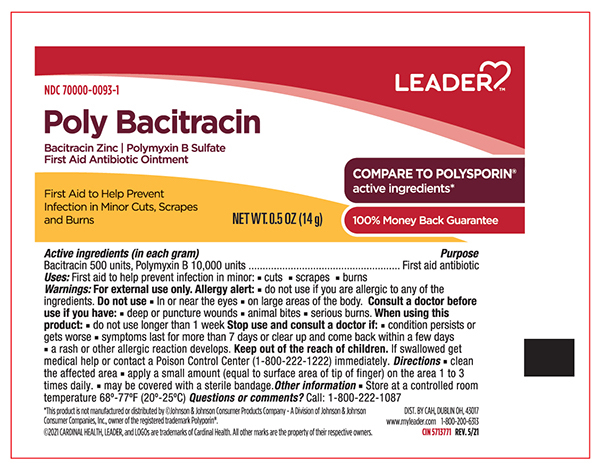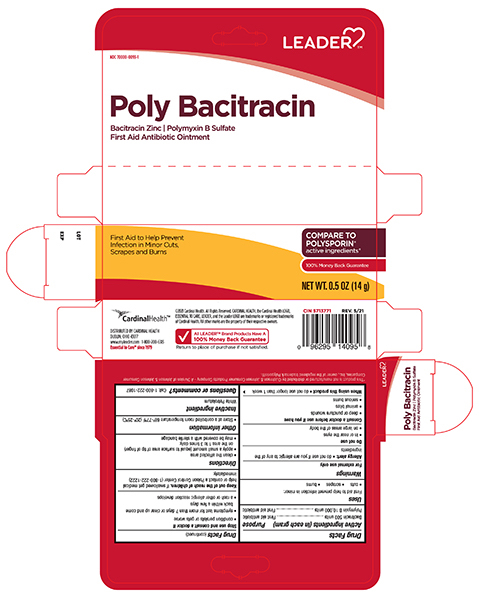 DRUG LABEL: Leader Poly Bacitracin
NDC: 70000-0093 | Form: OINTMENT
Manufacturer: Cardinal Health 110, Inc.
Category: otc | Type: HUMAN OTC DRUG LABEL
Date: 20240118

ACTIVE INGREDIENTS: Bacitracin Zinc 500 [USP'U]/1 g; POLYMYXIN B SULFATE 10000 [USP'U]/1 g
INACTIVE INGREDIENTS: Petrolatum

Leader Poly-Bacitracin

Drug Facts

Active ingredients (In each gram)

Bacitracin 500 units

Polymyxin B Sulfate 10,000 units

Purpose

First aid antibiotic

Uses

First aid to help prevent infection in minor:

- cuts
- scrapes
- burns

Warnings

For external use only

Allergy alert:

- do not use if you are allergic to any of the ingredients

Do not use

- in or near the eyes
- on large areas of the body

Consult a doctor before use if you have

- deep or puncture wounds
- animal bites
- serious burns

When using this product

- do not use longer than 1 week

Stop use and consult a doctor if

- condition persists or gets worse
- symptoms last for more than 7 days or clear up and come back within a few days
- a rash or other allergic reaction develops

KEEP OUT OF REACH OF CHILDREN

Keep out of the reach of children. If swallowed get medical help or contact a Poison Control Center immediately.

Directions

- clean the affected area
- apply a small amount (equal to surface area of tip of finger) on the area 1 to 3 times daily.
- may be covered with a sterile bandage

Other information

- Store at a controlled room temperature 20º-25ºC (68° to 77°F)

Inactive ingredient

Petrolatum

Principal Display Panel – Carton Label

Leader Major NDC 70000-0093-1

Poly Bacitracin Zinc Ointment USP

Bacitracin Zinc 500 units

Polymixin B sulfate 10,000 units

First Aid Antibiotic Ointment

NET WT. 0.5 oz (14g)

Principal Display Panel – Tube Label

Leader NDC 70000-0093-1

Poly Bacitracin Zinc Ointment

Bacitracin Zinc 500 Units

Polymixin B Sulfate 10,000 units

First Aid Antibiotic Ointment

Protection against Infection

NET WT. 0.5 oz (14g)